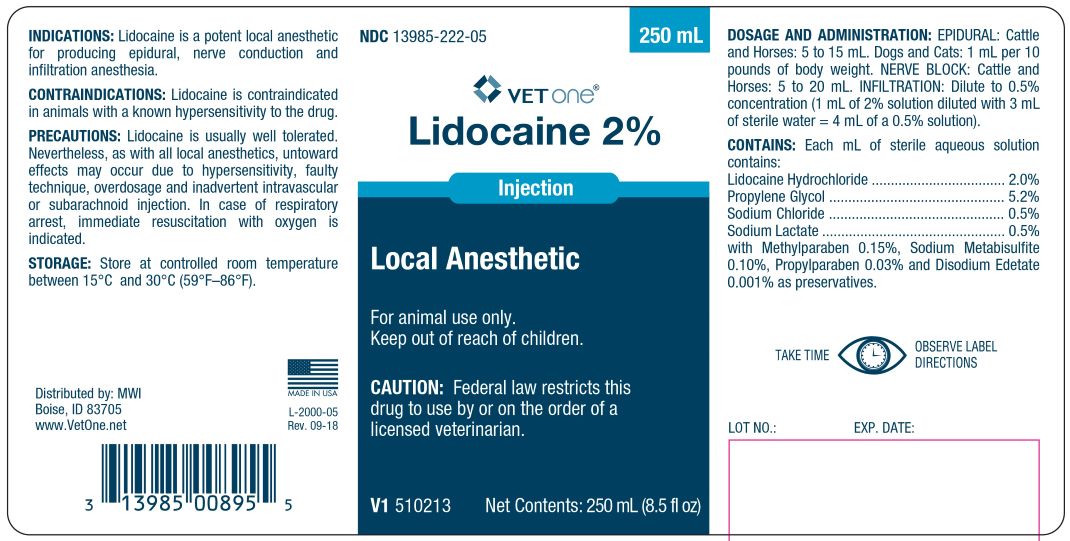 DRUG LABEL: Lidocaine
NDC: 13985-222 | Form: INJECTION
Manufacturer: MWI/VetOne
Category: animal | Type: PRESCRIPTION ANIMAL DRUG LABEL
Date: 20200214

ACTIVE INGREDIENTS: LIDOCAINE HYDROCHLORIDE 0.02 g/1 mL

Lidocaine 2% Injection Local Anesthetic

INDICATIONS AND USAGE

CAUTION: Federal law restricts this drug to use by or on the order of licensed veterinarian.

For animal use only.

Keep out of reach of children.

INDICATIONS

Lidocaine is a potent local anesthetic for producing epidural, nerve conduction and infiltration anesthesia.

CONTRAINDICATIONS

Lidocaine is contraindicated in animals with a known hypersensitivity to the drug.

PRECAUTIONS

Lidocaine is usually well tolerated. Nevertheless, as with all local anesthetics, untoward effects may occur due to hypersensitivity, faulty technique, overdosage and inadvertent intravascular or subarachnoid injection. In case of respiratory arrest, immediate resuscitation with oxygen is indicated.

CONTAINS

Each mL of sterile aqueous solution contains:
Lidocaine Hydrochloride ............. 2.0%
Propylene Glycol ....................... 5.2%
Sodium Chloride ........................ 0.5%
Sodium Lactate ......................... 0.5%

with Methylparaben 0.15%, Sodium Metabisulfite 0.10%,
Propylparaben 0.03%, Disodium Edetate 0.001% as preservatives.

DOSAGE AND ADMINISTRATION

EPIDURAL: Cattle and Horses: 5 to 15 mL. Dogs and Cats: 1 mL per 10 pounds of body weight.
NERVE BLOCK: Cattle and Horses: 5 to 20 mL
INFILTRATION: Dilute to 0.5% concentration (1 mL of 2% solution diluted with 3 mL of sterile water = 4 mL of a 0.5% solution).

STORAGE

Store at controlled room temperature between 15o and 30oC (59o-86oF)

TAKE TIME OBSERVE LABEL DIRECTIONS